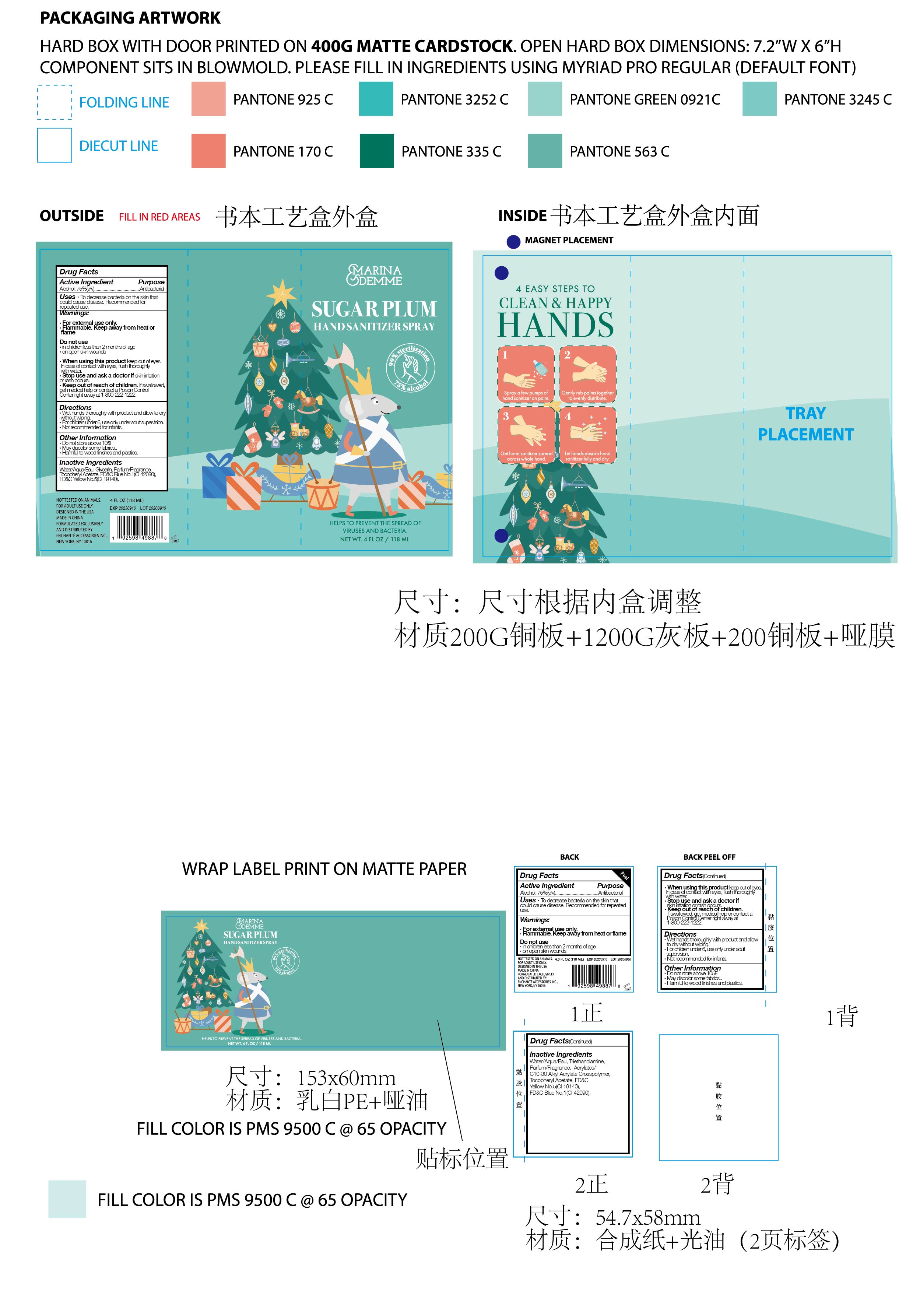 DRUG LABEL: MARINA DEMME SUGAR PLUM HAND SANITIZER
NDC: 50563-248 | Form: SPRAY
Manufacturer: ENCHANTE ACCESSORIES INC.
Category: otc | Type: HUMAN OTC DRUG LABEL
Date: 20200926

ACTIVE INGREDIENTS: ALCOHOL 75 mL/100 mL
INACTIVE INGREDIENTS: GLYCERIN; .ALPHA.-TOCOPHEROL ACETATE; FD&C BLUE NO. 1; WATER; FD&C YELLOW NO. 5

50563-248/ R80ABST3

Active Ingredient

Ethyl Alcohol: 75% (v/v)

Purpose

Antibacterial

Use

■ To decrease bacteria on the skin that could cause disease
■Recommended for repeated use

WARNINGS

For external use only, Hands

Flammable. Keep away from heat or flame

Do not use

in children less than two months of age

on open skin wounds

When using this product, keep out of eyes.
In case of contact with eyes, flush thoroughly with water

Stop Use

Stop use and ask a doctor if skin irritation or rash occurs

keep out of reach of children

Use under adult supervision. If swallowed, get medical help or contact a poison control center right away at 1-800-222-1222

Directions

Wet hands thoroughly with product and allow to dry without wiping

For children under 6, use only under adult supervision

Not recommended for infants

Other information

Do not store above 105F

May discolor some fabrics

Harmful to wood finishes and plastics

Inactive ingredients

Water, Glycerin, Parfum/Fragrance, Tocopheryl Acetate, FD&C Blue No.1 (CI 42090), FD&C Yellow No. 5 (CI 19140)